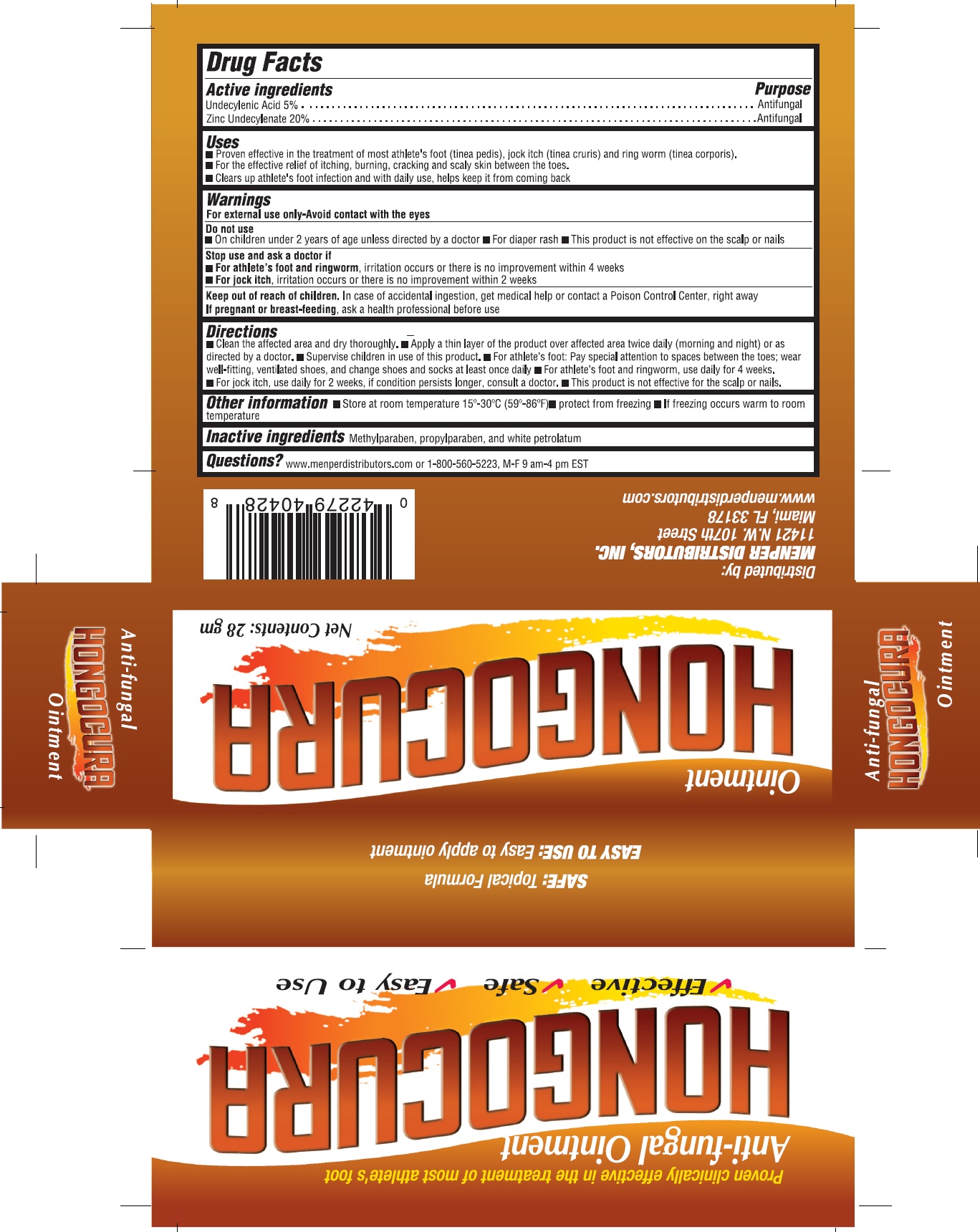 DRUG LABEL: Hongocura
NDC: 53145-017 | Form: OINTMENT
Manufacturer: MENPER DISTRIBUTORS, INC.
Category: otc | Type: HUMAN OTC DRUG LABEL
Date: 20250722

ACTIVE INGREDIENTS: UNDECYLENIC ACID 5 g/100 g; ZINC UNDECYLENATE 20 g/100 g
INACTIVE INGREDIENTS: METHYLPARABEN; PROPYLPARABEN; WHITE PETROLATUM

Hongocura ointment

Active Ingredients Purpose

Undecylenic Acid 5%...................Antifungal

Zinc Undecylenate 20%...............Antifungal

Purpose Antifungal

Uses:

Proven effective in the treatment of athlete's foot (tinea pedis),jock itch (tinea cruris) and ringworm (tinea corporis).
For the effective relief of itching, burning, crackling and scaly skin between toes.

Clears up athlete's foot infection and with daily use, helps keep it from coming back.

WARNINGS

Warning:for external use only- Avoid contact with the eyes

Do not use:

On children under 2 years of age, unless directed by a doctor. For diaper rash. This product is not effective on the scalp or nails.

Stop use and ask a doctor if:For athlete's foot and ringworm, if irritation occurs or if there is no improvement within 4 weeks. For jock itch, if irritation occurs or if there is no improvment within 2 weeks

KEEP OUT OF REACH OF CHILDREN

Keep away of reach of children. In case of accidental ingestion, get medical help or contact a Posion Control Center, right away.

PREGNANCY OR BREAST FEEDING

If pregnant or breast-feeding, ask a health professional before use.

Directions:

Clean the affected area and dry throughly. Apply a thin layer of the product over affected area twice daily (morning and night) or as directed by a doctor. Supervise children in use of this product. For athlete's foot: Pay special attention to spaces between the toes; wear well-fitting, ventilated shoes, and change shoes and socks at least once daily. For athlete's foot and ringworm, use daily for 4 weeks. For jock itch, use daily for 2 weeks, if condition persists longer, consult a doctor. This product is not effective for the scalp or nails.

INACTIVE INGREDIENT

Inactive ingredients: Methylparaben, propylparaben and white petrolatum

QUESTIONS

Questions? www.menperdistributors.com or 1-800-560-5223, M-F 9 am- 4 pm EST